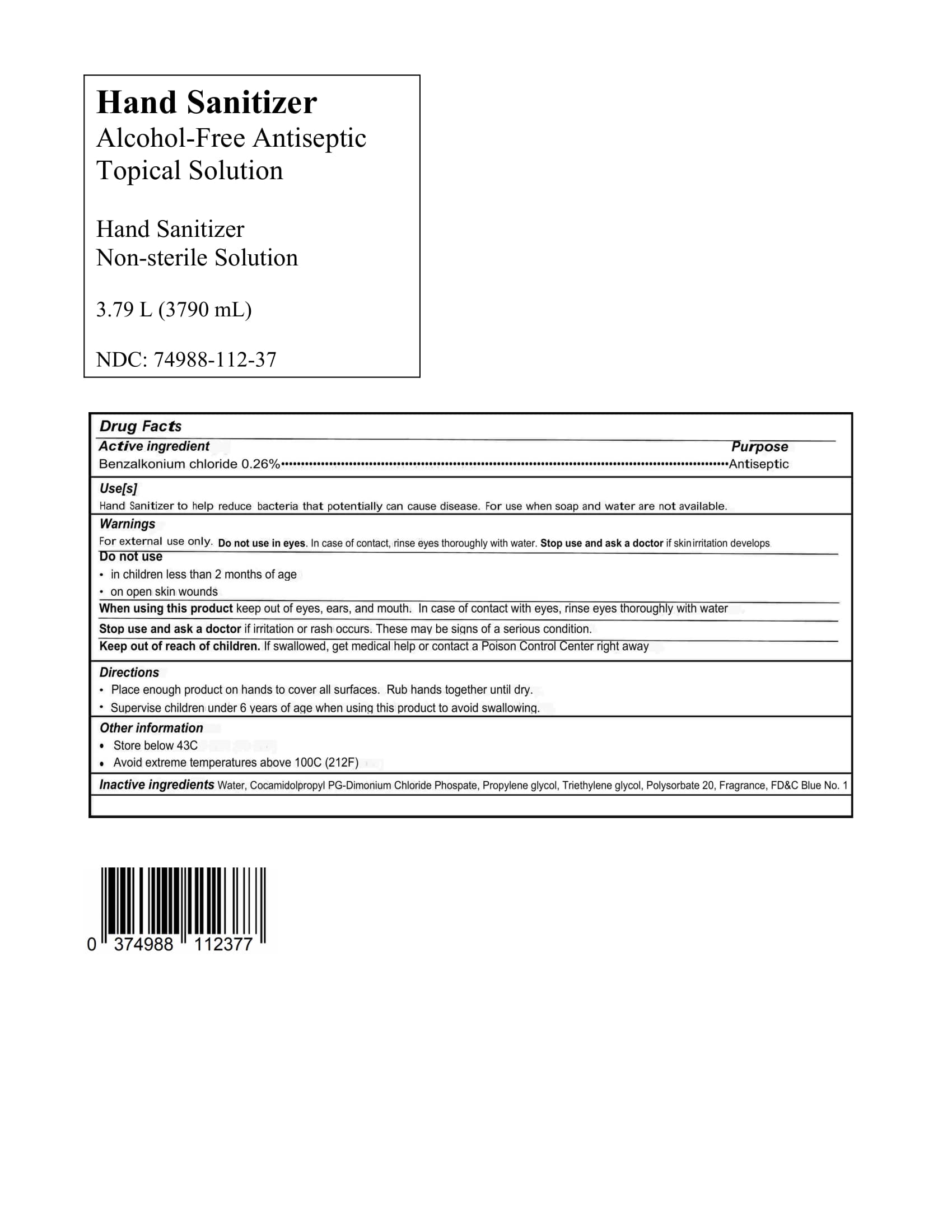 DRUG LABEL: Hand Sanitizer
NDC: 74988-112 | Form: LIQUID
Manufacturer: SanitizeNow Inc.
Category: otc | Type: HUMAN OTC DRUG LABEL
Date: 20200424

ACTIVE INGREDIENTS: BENZALKONIUM CHLORIDE 0.13 g/100 mL
INACTIVE INGREDIENTS: WATER; POLYSORBATE 20; COCAMIDOPROPYL PG-DIMONIUM CHLORIDE PHOSPHATE; TRIETHYLENE GLYCOL; FD&C BLUE NO. 1; PROPYLENE GLYCOL

Disclaimer: Most OTC drugs are not reviewed and approved by FDA, however they may be marketed if they comply with applicable regulations and policies. FDA has not evaluated whether this product complies.

The hand sanitizer is manufactured using only the following United States Pharmacopoeia (USP) grade ingredients in the preparation of the product:

1. Benzalkonium chloride 0.26%
2. Propylene glycol
3. Cocamidolpropyl PG-Dimonium Chloride Phospate
4. Sterile distilled water or boiled cold water.
5. Triethylene glycol
6. Polysorbate 20
7. Fragrance
8. FD&C Blue No. 1

The firm does not add other active or inactive ingredients. Different or additional ingredients may impact the quality and potency of the product.

Active Ingredient(s)

Benzalkonium chloride 0.26% Purpose: Antiseptic

Purpose

Antiseptic, Hand Sanitizer

Use

Hand Sanitizer to help reduce bacteria that potentially can cause disease. For use when soap and water are not available.

Warnings

For external use only.

Do not use

- in children less than 2 months of age
- on open skin wounds
- in eyes. In case of contact, rinse eyes thoroughly with water

When using this product keep out of eyes, ears, and mouth. In case of contact with eyes, rinse eyes thoroughly with water.
Stop use and ask a doctor if irritation or rash occurs. These may be signs of a serious condition.
Keep out of reach of children. If swallowed, get medical help or contact a Poison Control Center right away.

Stop use and ask a doctor if irritation or rash occurs.

Keep out of reach of children. If swallowed, get medical help or contact a Poison Control Center right away.

Directions

- Place enough product on hands to cover all surfaces. Rub hands together until dry.
- Supervise children under 6 years of age when using this product to avoid swallowing.

Other information

- Store below 43C
- Avoid extreme temperatures above 100C (212F)

Inactive ingredients

Water, Cocamidolpropyl PG-Dimonium Chloride Phospate, Propylene glycol, Triethylene glycol, Polysorbate 20, Fragrance, FD&C Blue No. 1

Package Label - Principal Display Panel

3790 mL NDC: 74988-112-37